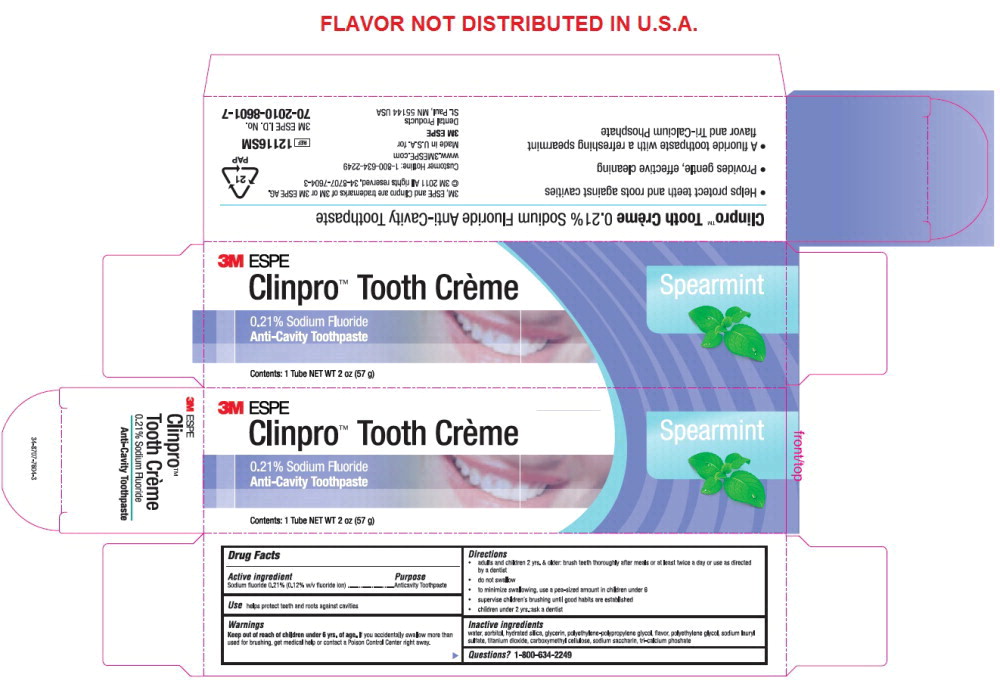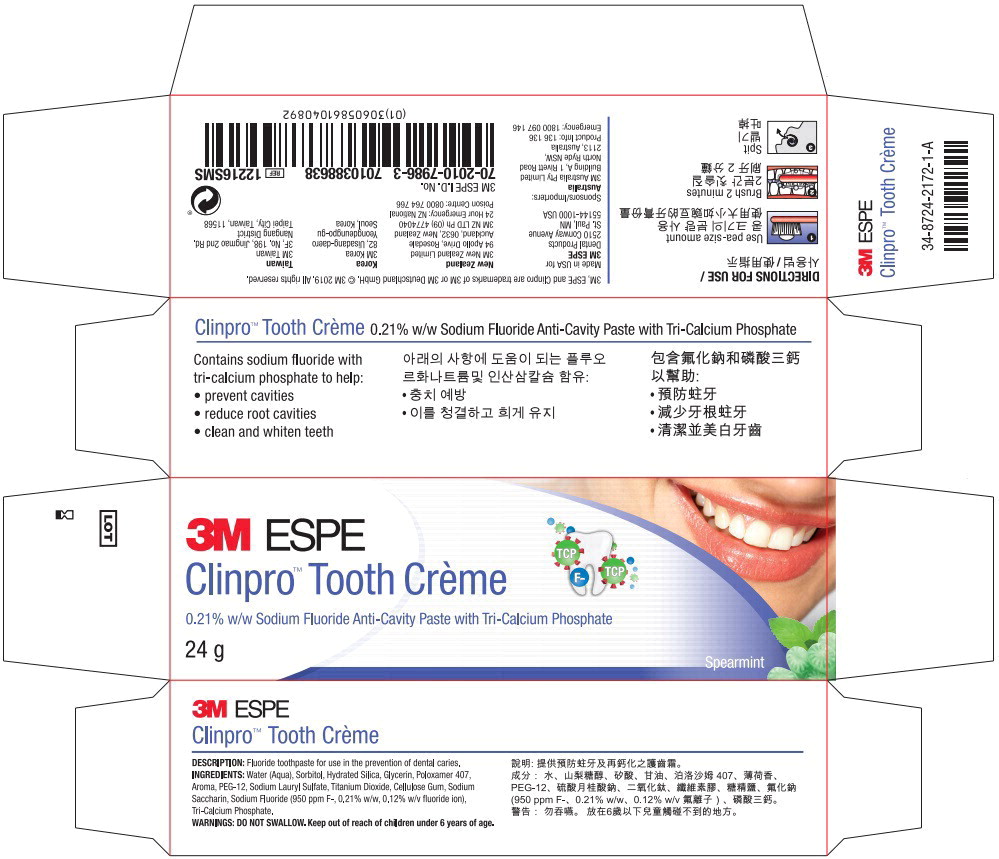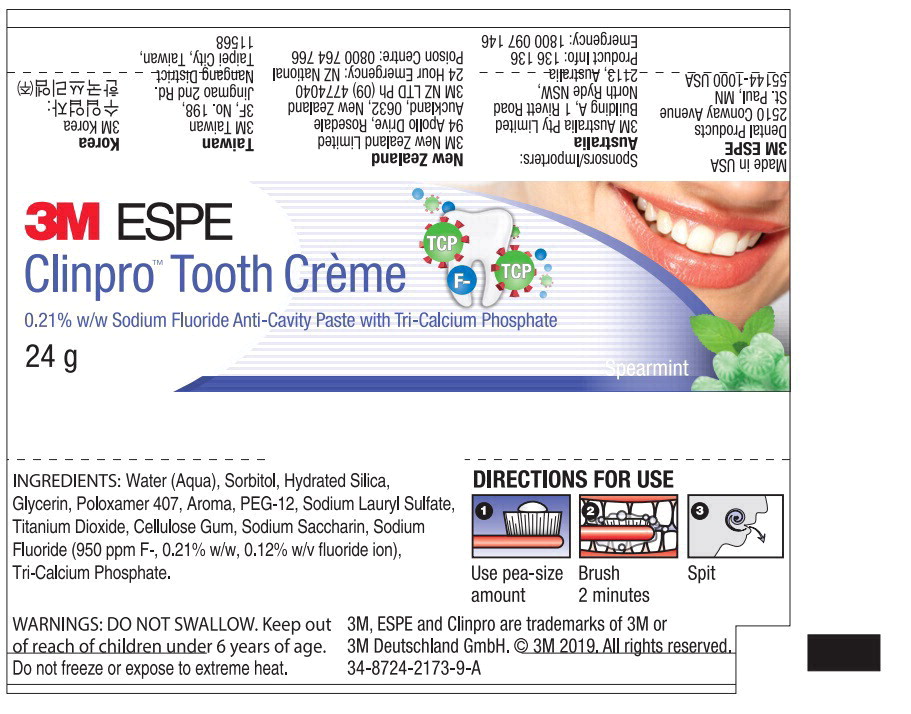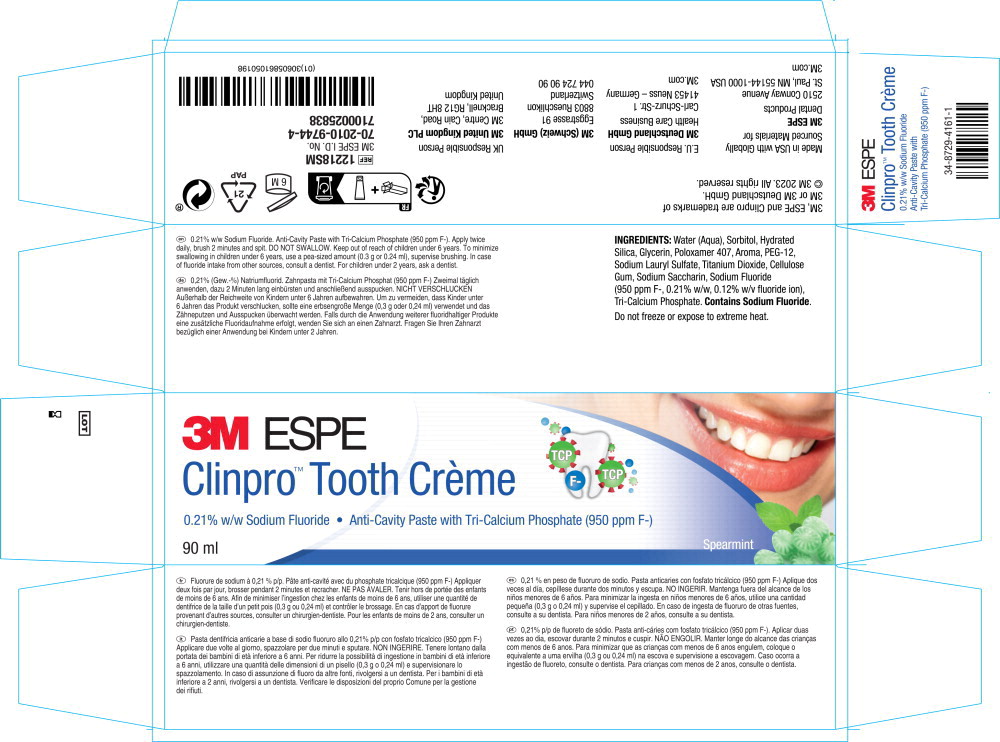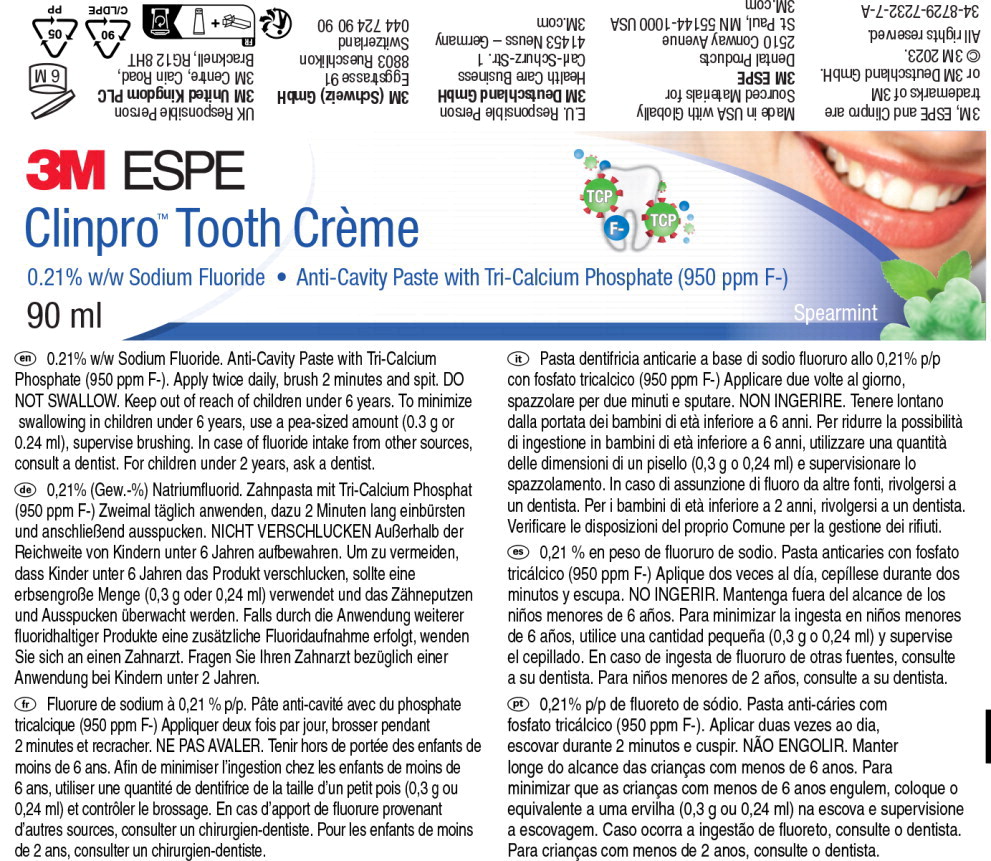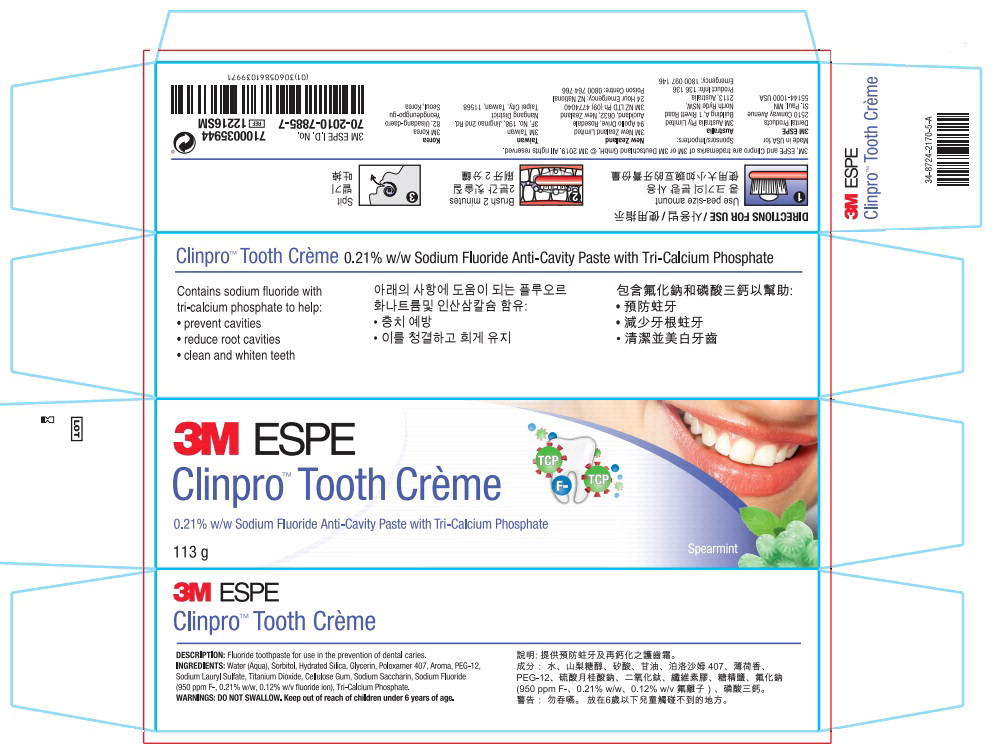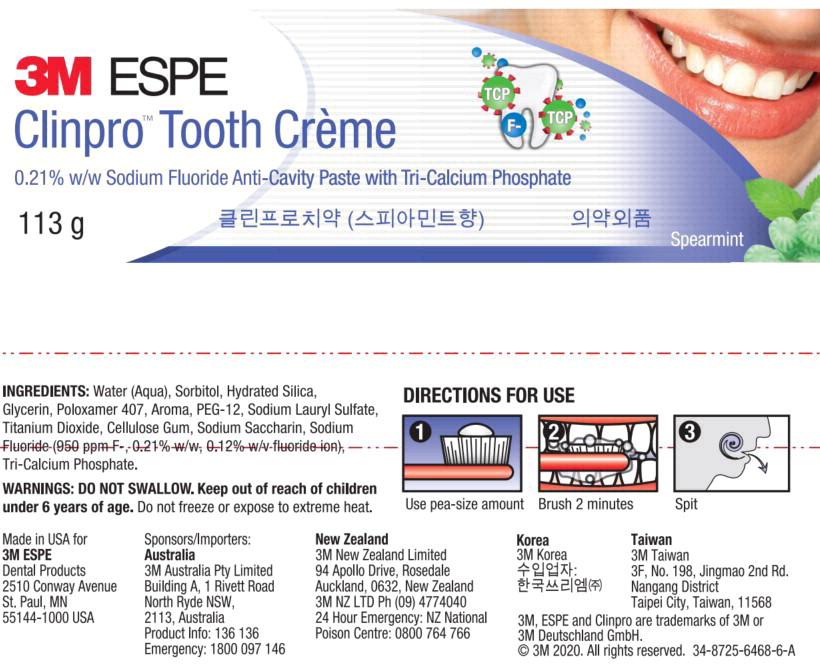 DRUG LABEL: Clinpro Tooth Creme
NDC: 48878-3170 | Form: PASTE, DENTIFRICE
Manufacturer: Solventum US LLC
Category: otc | Type: HUMAN OTC DRUG LABEL
Date: 20260108

ACTIVE INGREDIENTS: sodium fluoride 0.950 mg/1 g
INACTIVE INGREDIENTS: Water; Sorbitol; Silicon Dioxide; Glycerin; Polyethylene Glycol, Unspecified; Sodium Lauryl Sulfate; Titanium Dioxide; Carboxymethylcellulose Sodium; Saccharin Sodium; Tricalcium Phosphate

Drug Facts

Active ingredient

Sodium fluoride 0.21% (0.12% w/v fluoride ion)

Purpose

Anticavity Toothpaste

Use

Helps protect teeth and roots against cavities

Warnings

Keep out of reach of children under 6 years of age. If you accidentally swallow more than used for brushing, get medical help or contact a Poison Control Center right away.

Directions

- adults and children 2 years & older: brush teeth thoroughly after meals or at least twice a day or use as directed by a dentist
- do not swallow
- to minimize swallowing, use a pea-sized amount in children under 6
- supervise children's brushing until good habits are established
- children under 2 years: ask a dentist

Inactive ingredients

water, sorbitol, hydrated silica, glycerin, polyethylene-polypropylene glycol, flavor, polyethylene glycol, sodium lauryl sulfate, titanium dioxide, carboxymethyl cellulose, sodium saccharin, tri-calcium phosphate

Questions?

1-800-634-2249

Principal Display Panel - 57g Carton Label

3M ESPE

Clinpro™ Tooth Crème

Spearmint

0.21% Sodium Fluoride

Anti-Cavity Toothpaste

Contents: 1 Tube NET WT 2 oz (57 g)

Principal Display Panel - 24g Carton Label

3M ESPE

Clinpro™ Tooth Crème

0.21% w/w Sodium Fluoride Anti-Cavity Paste with Tri-Calcium Phosphate

24 g

Spearmint

Principal Display Panel - 24g Tube Label

3M ESPE

Clinpro™ Tooth Crème

0.21% w/w Sodium Fluoride Anti-Cavity Paste with Tri-Calcium Phosphate

24 g

Spearmint

Principal Display Panel - 90 mL Carton Label

3M ESPE

Clinpro™ Tooth Crème

0.21% w/w Sodium Fluoride Anti-Cavity Paste with Tri-Calcium Phosphate (950 ppm F-)

90 ml

Spearmint

Principal Display Panel - 90 mL Tube Label

3M ESPE

Clinpro™ Tooth Crème

0.21% w/w Sodium Fluoride Anti-Cavity Paste with Tri-Calcium Phosphate (950 ppm F-)

90 ml

Spearmint

Principal Display Panel - 113g Carton Label

3M ESPE

Clinpro™ Tooth Crème

0.21% w/w Sodium Fluoride Anti-Cavity Paste with Tri-Calcium Phosphate

113 g

Spearmint

Principal Display Panel - 113g Tube Label

3M ESPE

Clinpro™ Tooth Crème

0.21% w/w Sodium Fluoride Anti-Cavity Paste with Tri-Calcium Phosphate

113 g

Spearmint